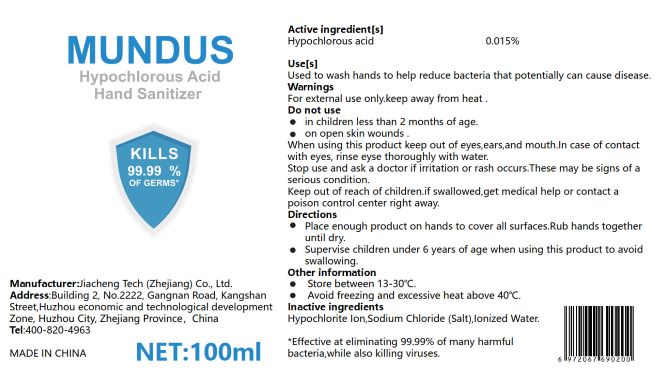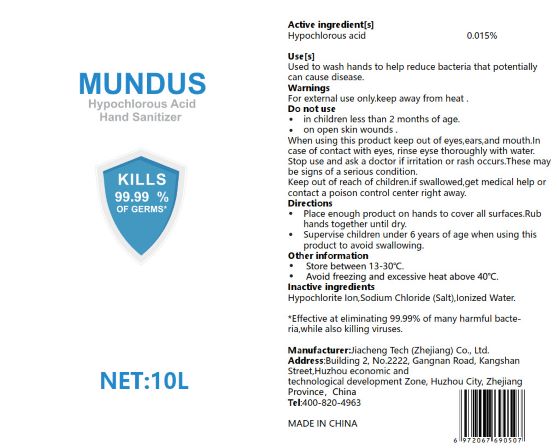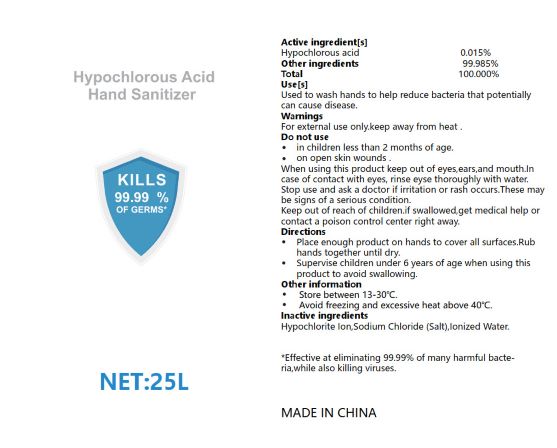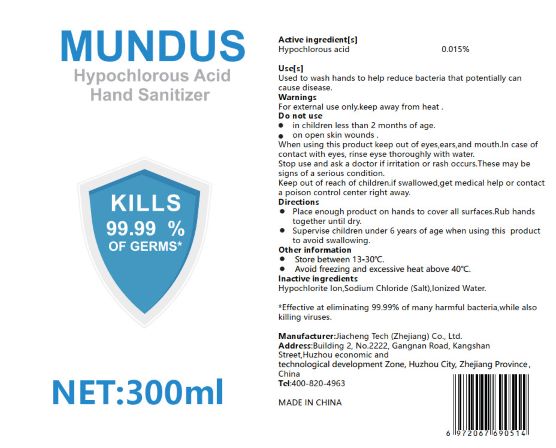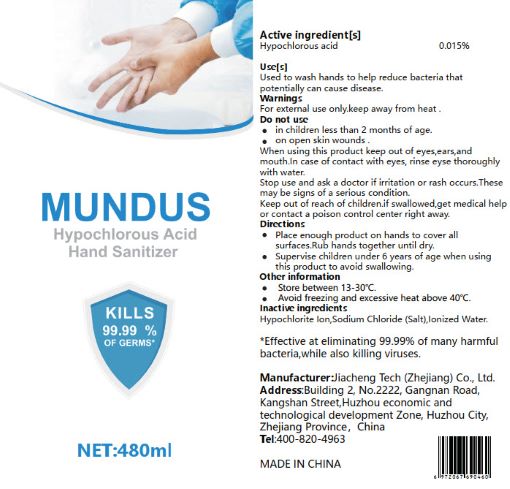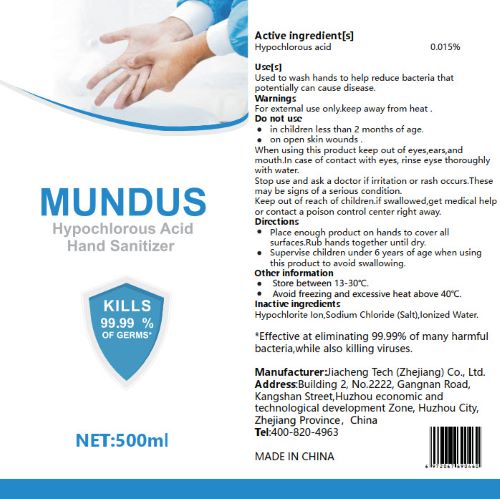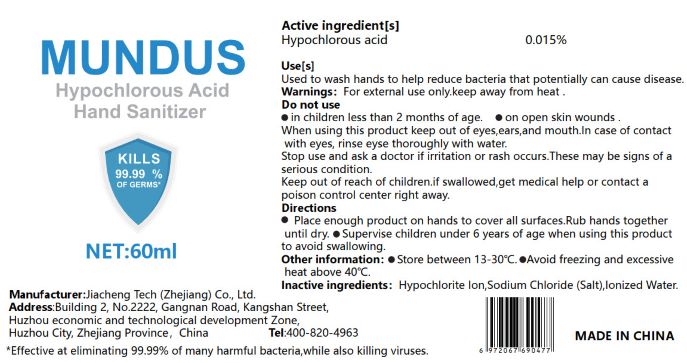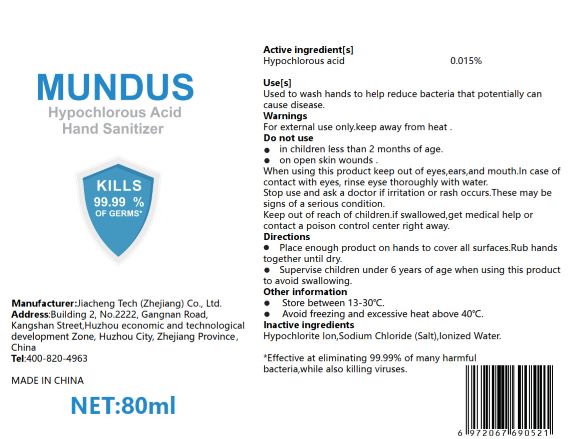 DRUG LABEL: Mundus Hypochlorous Acid Hand Sanitizer
NDC: 55683-003 | Form: LIQUID
Manufacturer: Jiacheng Tech (Zhejiang) Co., Ltd.
Category: otc | Type: HUMAN OTC DRUG LABEL
Date: 20220314

ACTIVE INGREDIENTS: HYPOCHLOROUS ACID 0.015 g/100 mL
INACTIVE INGREDIENTS: SODIUM CHLORIDE; HYPOCHLORITE ION; WATER

Mundus Hypochlorous Acid Hand Sanitizer
55683-002-01 480ml
55683-002-02 100ml
55683-002-03 25L
55683-002-04 10L
55683-002-05 60ml
55683-002-06 80ml
55683-002-07 300ml
55683-002-08 500ml

Active Ingredient(s)

Hypochlorous acid 0.015%

Purpose

Antiseptic, Hand Sanitizer

Use

Used to wash hands to help reduce bacteria that potentially can cause disease.

Warnings

- For external use only.
- Keep away from heat.

Do not use

- in children less than 2 months of age.
- on open skin wounds.

When using this product keep out of eyes, ears, and mouth. In case of contact with eyes, rinse eyes thoroughly with water.

Stop use and ask a doctor if irritation or rash occurs. These may be signs of a serious condition.

Keep out of reach of children. if swallowed, ger medical help or contact a poison control center right away.

Directions

- Place enough product on hands to cover all surfaces. Rub hands together until dry.
- Supervise children under 6 years of age when using this product to avoid swallowing.

Other information

- Store between 13-30℃.
- Avoid freezing and excessive heat above 40℃.

Inactive ingredients

Hypochlorite Ion, Sodium Chloride(Salt), lonized Water.

Package Label - Principal Display Panel

480 mL NDC: 55683-003-01

100 mL NDC: 55683-003-02

25000 mL NDC: 55683-003-03

10000 mL NDC: 55683-003-04

60 mL NDC: 55683-003-05

80 mL NDC: 55683-003-06

300 mL NDC: 55683-003-07

500 mL NDC: 55683-003-08